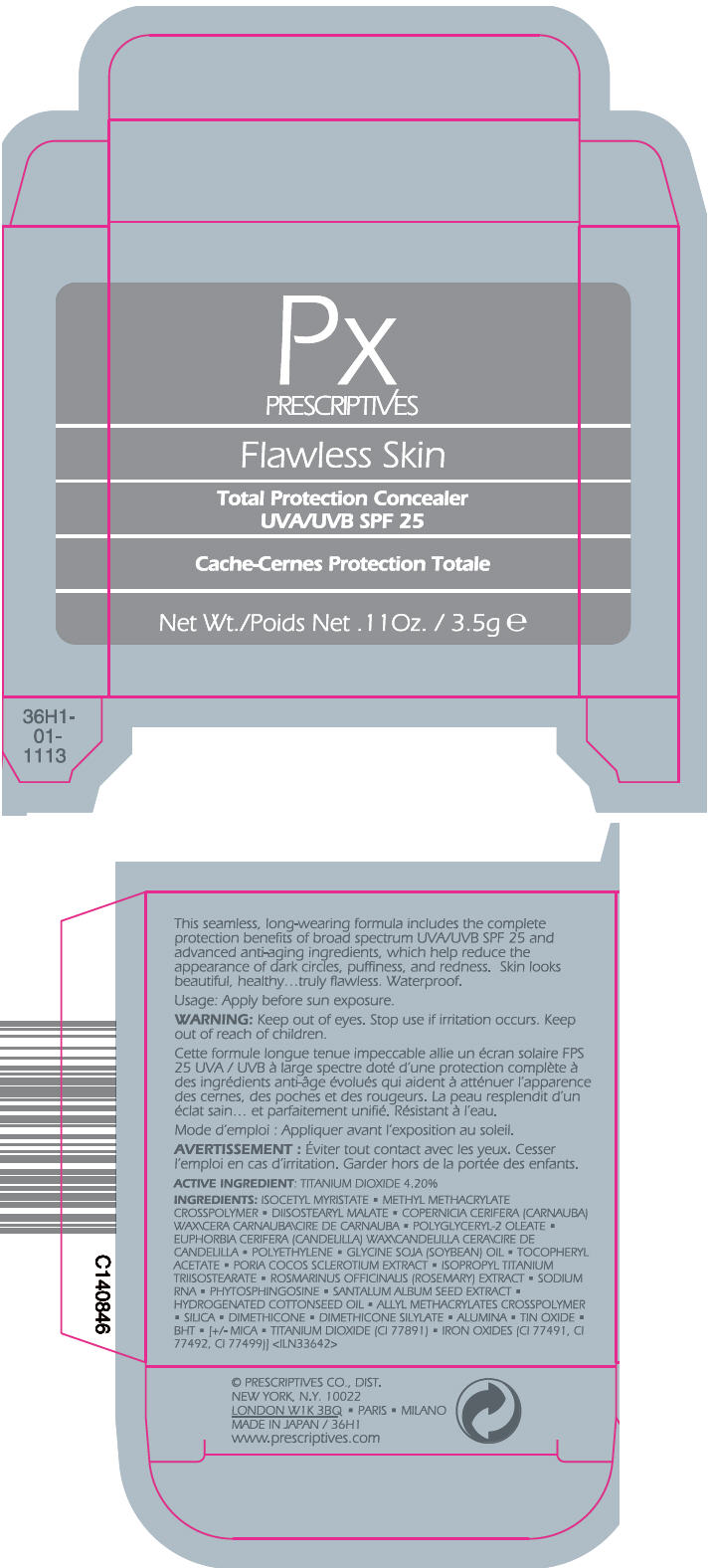 DRUG LABEL: FLAWLESS SKIN TOTAL PROTECTION CONCEALER SPF 25
NDC: 59158-914 | Form: PASTE
Manufacturer: PRESCRIPTIVES INC
Category: otc | Type: HUMAN OTC DRUG LABEL
Date: 20120911

ACTIVE INGREDIENTS: TITANIUM DIOXIDE 4.2 g/100 g
INACTIVE INGREDIENTS: ISOCETYL MYRISTATE; DIISOSTEARYL MALATE; CARNAUBA WAX; CANDELILLA WAX; HIGH DENSITY POLYETHYLENE; SOYBEAN OIL; .ALPHA.-TOCOPHEROL ACETATE; ISOPROPYL TITANIUM TRIISOSTEARATE; ROSEMARY; PHYTOSPHINGOSINE; SANTALUM ALBUM SEED; HYDROGENATED COTTONSEED OIL; SILICON DIOXIDE; DIMETHICONE; ALUMINUM OXIDE; STANNIC OXIDE; BUTYLATED HYDROXYTOLUENE; MICA; FERRIC OXIDE RED; FERRIC OXIDE YELLOW; FERROSOFERRIC OXIDE

FLAWLESS SKIN TOTAL PROTECTION CONCEALER SPF 25

Usage

Apply before sun exposure.

WARNING

Keep out of eyes.

Stop use if irritation occurs.

Keep out of reach of children.

ACTIVE INGREDIENT

TITANIUM DIOXIDE 4.20%

INGREDIENTS

ISOCETYL MYRISTATE • METHYL METHACRYLATE CROSSPOLYMER • DIISOSTEARYL MALATE • COPERNICIA CERIFERA (CARNAUBA) WAX\CERA CARNAUBA\CIRE DE CARNAUBA • POLYGLYCERYL-2 OLEATE • EUPHORBIA CERIFERA (CANDELILLA) WAX\CANDELILLA CERA\CIRE DE CANDELILLA • POLYETHYLENE • GLYCINE SOJA (SOYBEAN) OIL • TOCOPHERYL ACETATE • PORIA COCOS SCLEROTIUM EXTRACT • ISOPROPYL TITANIUM TRIISOSTEARATE • ROSMARINUS OFFICINALIS (ROSEMARY) EXTRACT • SODIUM RNA • PHYTOSPHINGOSINE • SANTALUM ALBUM SEED EXTRACT • HYDROGENATED COTTONSEED OIL • ALLYL METHACRYLATES CROSSPOLYMER • SILICA • DIMETHICONE • DIMETHICONE SILYLATE • ALUMINA • TIN OXIDE • BHT • [+/- MICA • TITANIUM DIOXIDE (CI 77891) • IRON OXIDES (CI 77491, CI 77492, CI 77499)] <ILN33642>

PRESCRIPTIVES CO., DIST.
NEW YORK, N.Y. 10022

PRINCIPAL DISPLAY PANEL - 3.5g Container Carton

PX
PRESCRIPTIVES

Flawless Skin

Total Protection Concealer
UVA/UVB SPF 25

Net Wt./Poids Net . 11 Oz. / 3.5g e